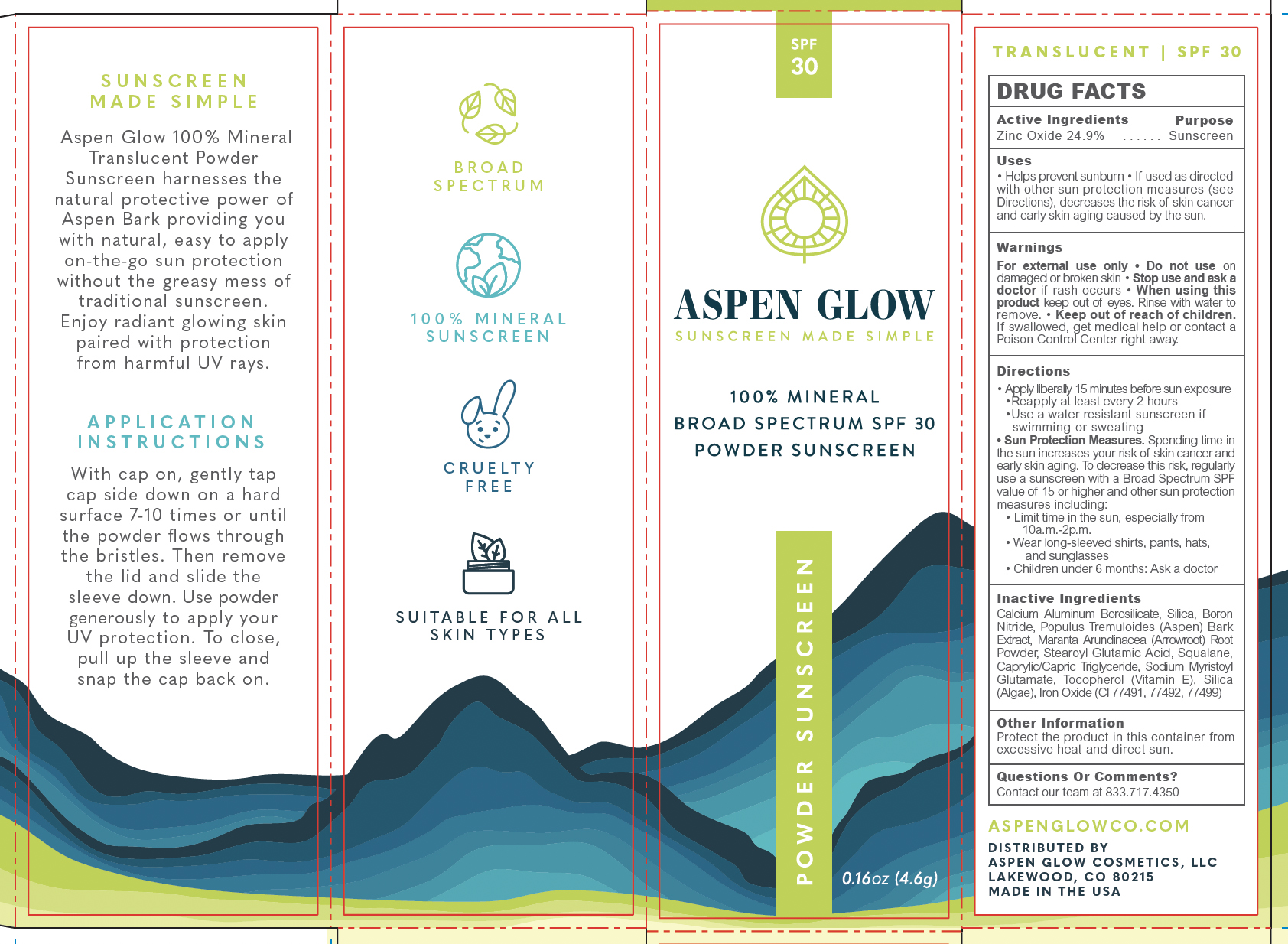 DRUG LABEL: Aspen Glow 100% Mineral Broad Spectrum SPF 30 Powder Sunscreen 0.16 oz / 4.6 g
NDC: 83512-0008 | Form: POWDER
Manufacturer: Aspen Glow Cosmetics, LLC
Category: otc | Type: HUMAN OTC DRUG LABEL
Date: 20251110

ACTIVE INGREDIENTS: ZINC OXIDE 24.9 g/100 g
INACTIVE INGREDIENTS: SILICON DIOXIDE; BORON NITRIDE; STEAROYL GLUTAMIC ACID; SQUALANE; CALCIUM ALUMINUM BOROSILICATE; POPULUS TREMULOIDES BARK; SODIUM MYRISTOYL GLUTAMATE; FERRIC OXIDE RED; MEDIUM-CHAIN TRIGLYCERIDES; TOCOPHEROL; MARANTA ARUNDINACEA ROOT

Aspen Glow Powder Sunscreen SPF 30 0.16 oz / 4.6 g

Active ingredient

Zinc Oxide 24.9%

Purpose

Sunscreen

Uses

Helps prevent sunburn

If used as directed with other sun protection measures (see Directions), decreases the risk of skin cancer and early skin aging caused by the sun

Warnings

- For external use only

Do not use

on damaged or broken skin

Stop use and ask a doctor

if rash occurs

When using this product

keep out of eyes. Rinse with water to remove.

Keep out of reach of children.

If swallowed, get medical help or contact a Poison Control Center right away.

Directions

Apply liberally 15 minutes before sun exposure

- Reapply at least every 2 hours
- Use a water resistant sunscreen if swimming or sweating

Sun Protection Measures. Spending time in the sun increases your risk of skin cancer and early skin aging. To decrease this risk, regularly use a sunscreen with a Broad Spectrum SPF value of 15 or higher and other sun protection measures including:

- Limit time in the sun, especially from 10 a.m. - 2 p.m.
- Wear long-sleeved shirts, pants, hats, and sunglasses
- Children under 6 months: Ask a doctor

Inactive ingredients

Calcium Aluminum Borosilicate, Silica, Boron Nitride, Populus Tremuloides (Aspen) Bark Extract, Maranta Arundinacea (Arrowroot) Root Powder, Stearoyl Glutamic Acid, Squalane, Caprylic/Capric Triglyceride, Sodium Myristoyl Glutamate, Tocopherol (Vitamin E), Silica (Algae), Iron Oxide (CI 7749, 77492, 77499)

Other information

Protect the product in this container from excessive heat and direct sun.

Questions or Comments?

Contact our team at 833.717.4350

Principal Display Panel

SPF 30

ASPEN GLOW

SUNSCREEN MADE SIMPLE

100% MINERAL

BROAD SPECTRUM SPF 30

POWDER SUNSCREEN

0.16oz (4.6g)

POWDER SUNSCREEN